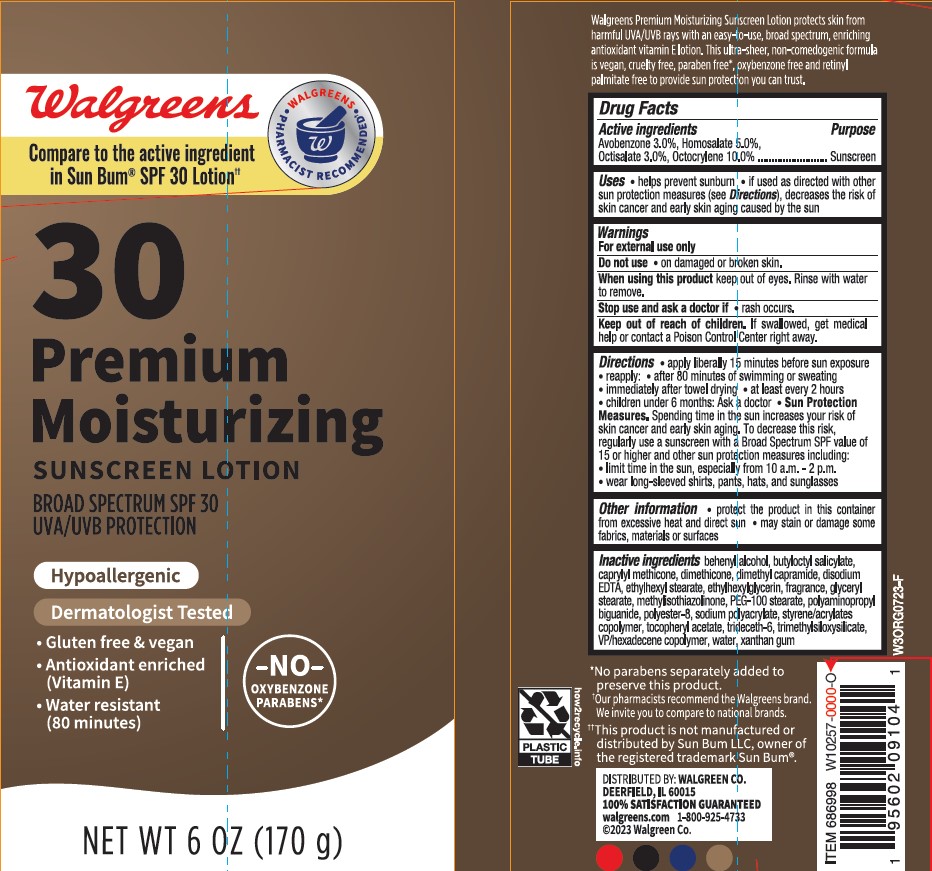 DRUG LABEL: Walgreens SPF 30 Premium Moisturizing Sunscreen
NDC: 0363-0280 | Form: LOTION
Manufacturer: WALGREEN COMPANY
Category: otc | Type: HUMAN OTC DRUG LABEL
Date: 20231121

ACTIVE INGREDIENTS: OCTOCRYLENE 100 mg/1 g; OCTISALATE 30 mg/1 g; HOMOSALATE 50 mg/1 g; AVOBENZONE 30 mg/1 g
INACTIVE INGREDIENTS: BUTYLOCTYL SALICYLATE; SODIUM POLYACRYLATE (8000 MW); ETHYLHEXYL STEARATE; TRIDECETH-6; PEG-100 STEARATE; XANTHAN GUM; BUTYL METHACRYLATE/METHYL METHACRYLATE/METHACRYLIC ACID/STYRENE CROSSPOLYMER; EDETATE DISODIUM; GLYCERYL MONOSTEARATE; WATER; DIMETHYL CAPRAMIDE; DOCOSANOL; TRIMETHYLSILOXYSILICATE (M/Q 0.8-1.0); METHYLCHLOROISOTHIAZOLINONE; POLIHEXANIDE HYDROCHLORIDE; POLYESTER-8 (1400 MW, CYANODIPHENYLPROPENOYL CAPPED); .ALPHA.-TOCOPHEROL ACETATE; VINYLPYRROLIDONE/HEXADECENE COPOLYMER; ETHYLHEXYLGLYCERIN; CAPRYLYL TRISILOXANE

Walgreens SPF 30 Premium Moisturizing Sunscreen Lotion

Active ingredients

Avobenzone 3.0%, Homosalate 5.0%, Octisalate 3.0%, Octocrylene 10.0%

Purpose

Sunscreen

Uses

- helps prevent sunburn
- if used as directed with other sun protection measures (see Directions), decreases the risk of skin cancer and early skin aging caused by the sun

Warnings

For external use only

Do not use

on damaged or broken skin

When using this product

keep out of eyes. Rinse with water to remove.

Stop use and ask a doctor

if rash occurs.

Keep out of reach of children.

If product is swallowed, get medical help or contact a Poison Control Center right away.

Directions

• apply liberally 15 minutes before sun exposure
• reapply:
• after 80 minutes of swimming or sweating
• immediately after towel drying
• at least every 2 hours
• Sun Protection Measures. Spending time in the sun increases your risk of skin cancer and early skin aging. To decrease this risk, regularly use a sunscreen with a Broad Spectrum SPF value of 15 or higher and other sun protection measures including:
• limit time in the sun, especially from 10 a.m. - 2 p.m.
• wear long-sleeved shirts, pants, hats, and sunglasses
• children under 6 months: Ask a doctor

Other information

• protect the product on this container from excessive heat and direct sun
• may stain or damage some fabrics, materials or surfaces

Inactive ingredients

behenyl alcohol, butyloctyl salicylate, caprylyl methicone, dimethicone, dimethyl capramide, disodium EDTA, ethylhexyl stearate, ethylhexylglycerin, fragrance, glyceryl stearate, methylisothiazolinone, PEG-100 stearate, polyaminopropyl biguanide, polyester-8, sodium polyacrylate, styrene/acrylates copolymer, tocopheryl acetate, trideceth-6, trimethylsiloxysilicate, VP/hexadecene copolymer, water, xanthan gum